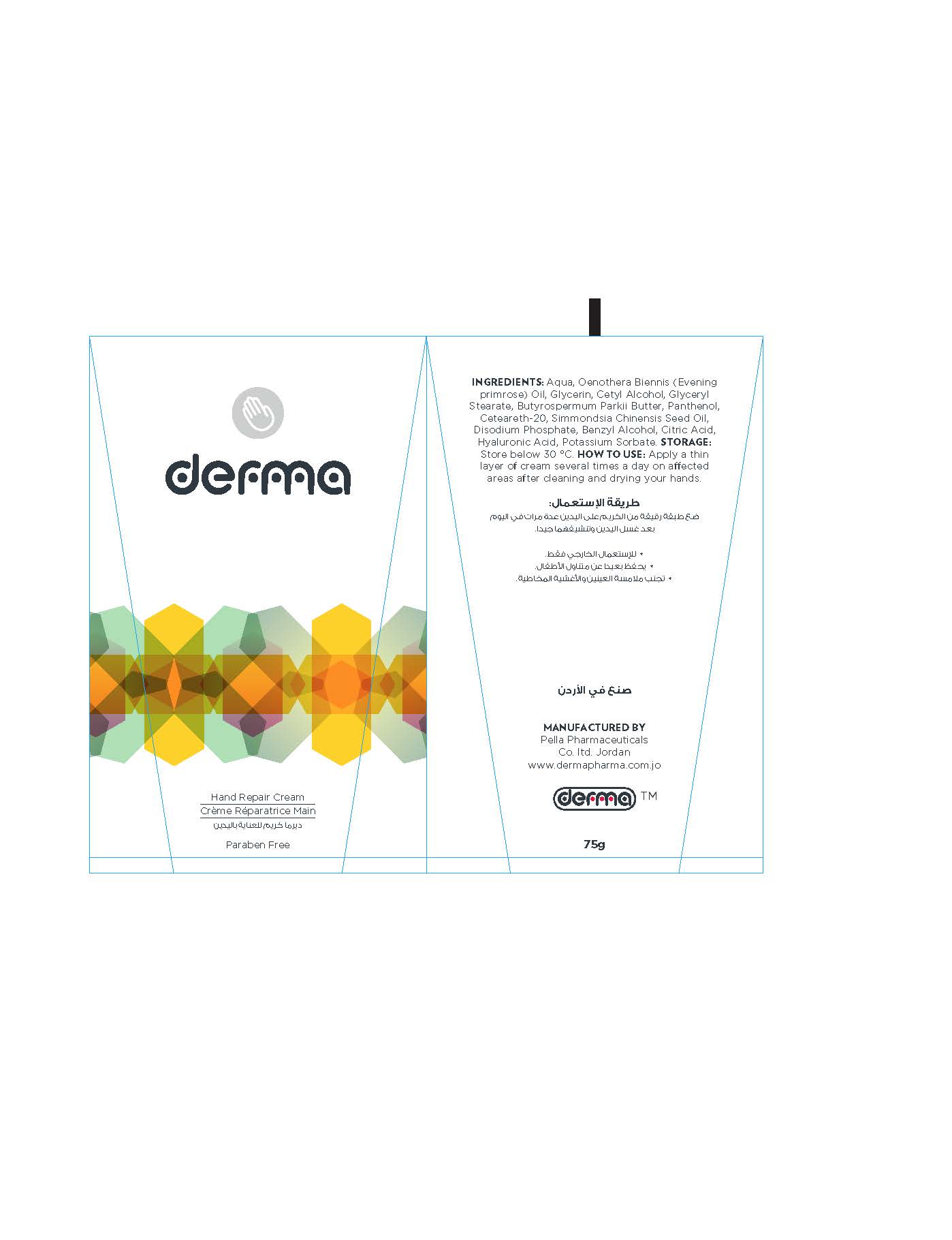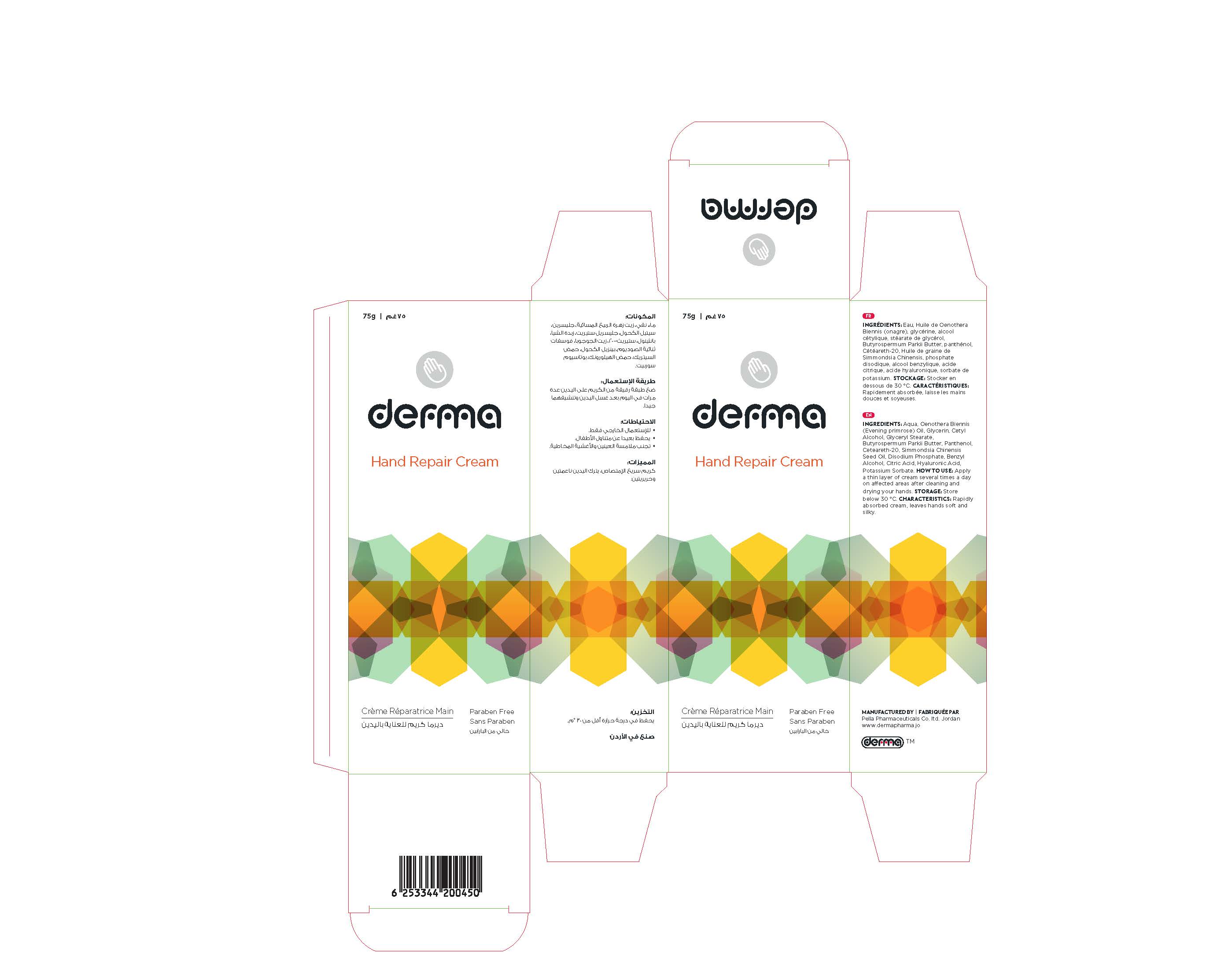 DRUG LABEL: Derma Hand Repair
NDC: 82160-450 | Form: CREAM
Manufacturer: Pella Pharmaceuticals Co. Ltd
Category: otc | Type: HUMAN OTC DRUG LABEL
Date: 20211202

ACTIVE INGREDIENTS: HYALURONIC ACID 0.75 mg/75 g; DEXPANTHENOL 22.5 mg/75 g
INACTIVE INGREDIENTS: ANHYDROUS CITRIC ACID; GLYCERIN; CETYL ALCOHOL; SHEA BUTTER; JOJOBA OIL; BENZYL ALCOHOL; WATER; GLYCERYL MONOSTEARATE; SODIUM PHOSPHATE, DIBASIC; POTASSIUM SORBATE; EVENING PRIMROSE OIL; POLYOXYL 20 CETOSTEARYL ETHER

Hand Repair

Forms and presentation

Cream: Tube of 75 g.

Active Ingredients

Panthenol

Hyaluronic Acid

Inactive ingredients

Aqua, Oenothera Biennis (Evening primrose) Oil, Glycerin, Cetyl Alcohol, Glyceryl Stearate, Butyrospermum Parkii Butter, Ceteareth-20, Simmondsia Chinensis (Jojoba) Seed Oil, Disodium Phosphate, Benzyl Alcohol, Citric Acid, Potassium Sorbate.

Purpose

Moisturizer

Properties

Derma Hand Repair cream has a synergistic combination of carefully selected natural oils and is rich in other moisturizing ingredients to promote cell regeneration of the damaged skin of hand.
Derma Hand Repair cream characterize by Non-greasy texture, nonsticky, rapidly absorbed, leaves hands soft and silky.
Paraben free.

Indications

Derma Hand Repair nourishes your hands with panthenol, Oenothera Biennis (Evening primrose) Oil and other natural oils that regenerate and strengthen your skin against external influences. Therefore it will smooth and moisturize rough, stressed and damaged hands.

Precautions

Keep out of reach of children

Warnings

- For external use only
- Avoid contact with eyes and mucous membrans

Contraindications

Hypersensitivity to any of the components.

Side effects

There are no known side effects.

Dosage and administration

Apply a thin layer of cream several times a day on affected areas after cleaning and drying your hands.

Storage conditions

Store at a temperature below 30 °C.